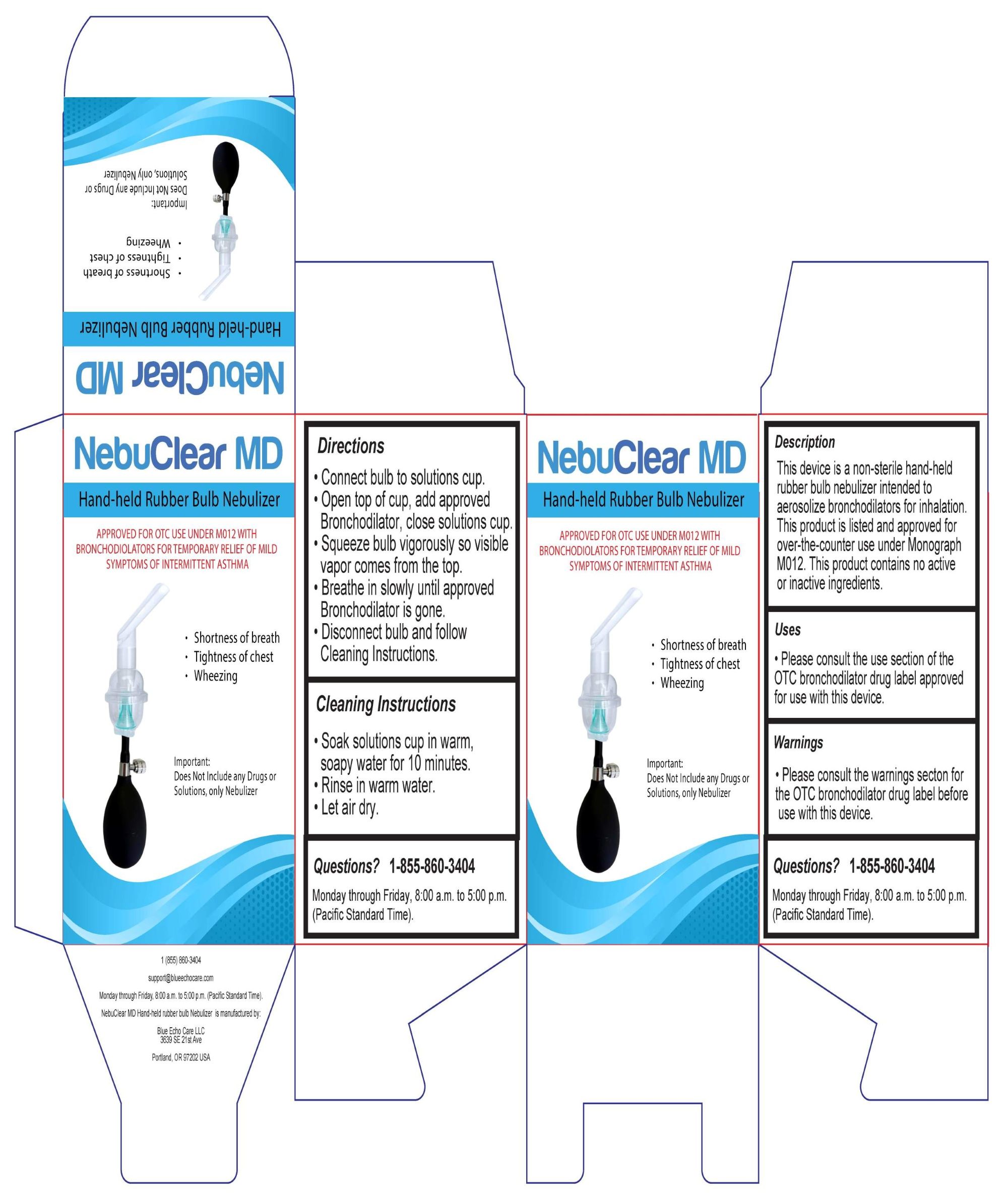 DRUG LABEL: Device - NebuClear MD Hand-held Rubber Bulb Nebulizer
NDC: 73117-521 | Form: AEROSOL, SPRAY
Manufacturer: Blue Echo Care LLC
Category: otc | Type: HUMAN OTC DRUG LABEL
Date: 20251118

ACTIVE INGREDIENTS: RACEPINEPHRINE HYDROCHLORIDE 11.25 mg/0.5 mL
INACTIVE INGREDIENTS: WATER

Description

This device is a non-sterile hand-held rubber bulb nebulizer intended to aerosolize bronchodilators for inhalation.

This product is listed and approved for over-the-counter use under Monograph M012.

This product contains no active or inactive ingredients.

Uses

Please consult the use section of the OTC bronchodilator drug label approved for use with this device.

Warnings

Please consult the warnings secton for the OTC bronchodilator drug label before use with this device.

PURPOSE

Please consult the purpose section of the OTC bronchodilator drug label approved for use with this device.

INACTIVE INGREDIENT

This is the device only and includes no active or inactive ingredients.

Keep out of reach of small children

Directions

- Connect bulb to solutions cup.
- Open top of cup, add approved Bronchodilator, close solutions cup.
- Squeeze bulb vigorously so visible vapor comes from the top.
- Breathe in slowly until approved Bronchodilator is gone.
- Disconnect bulb and follow Cleaning Instructions.

Cleaning Instructions

- Soak solutions cup in warm, soapy water for 10 minutes.
- Rinse in warm water.
- Let air dry.